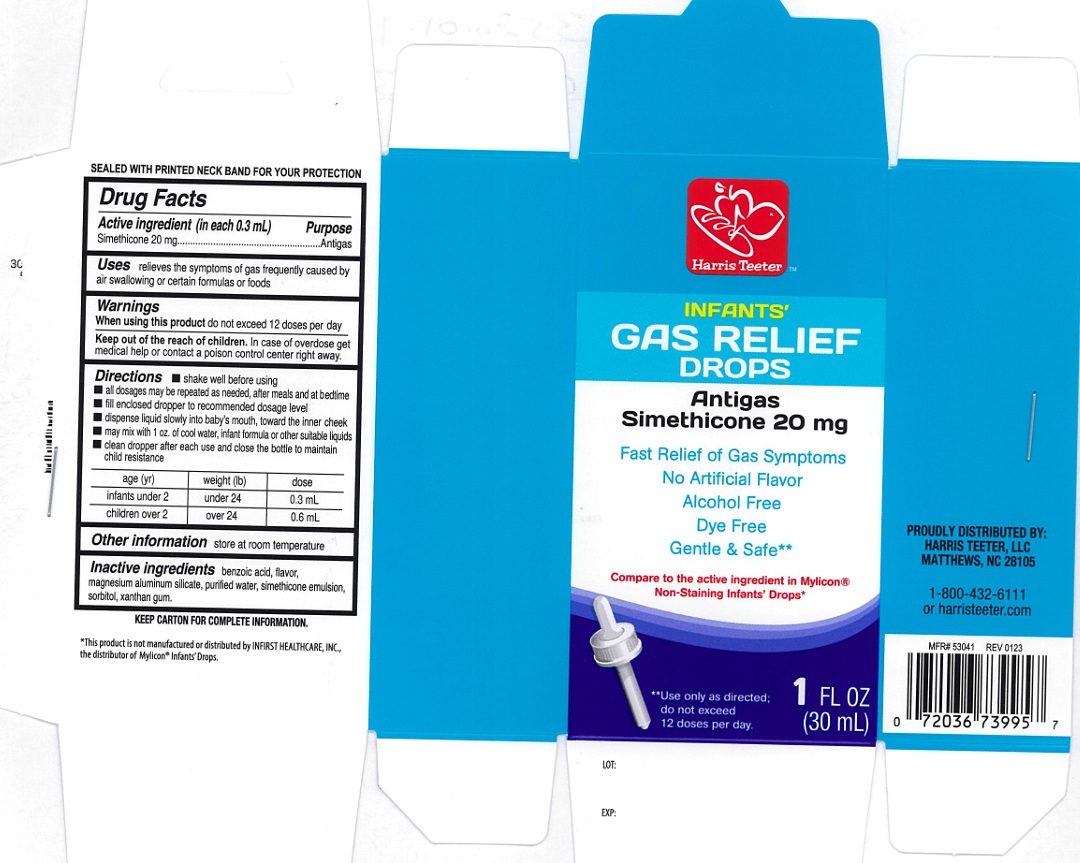 DRUG LABEL: Infants Gas relief
NDC: 69256-520 | Form: SOLUTION/ DROPS
Manufacturer: Harris Teeter, LLC
Category: otc | Type: Human OTC Drug Label
Date: 20250205

ACTIVE INGREDIENTS: DIMETHICONE 20 mg/0.3 mL
INACTIVE INGREDIENTS: BENZOIC ACID; MAGNESIUM ALUMINUM SILICATE; WATER; SORBITOL; XANTHAN GUM

Infants anti gas

ACTIVE INGREDIENT (in each 0.3 mL)

Simethicone 20 mg

PURPOSE

Antigas

USE(S)

relieves the symptoms of gas frequently caused by air swallowing or certain formulas or foods

WARNINGS

When using this product do not exceed 12 doses per day

KEEP OUT OF REACH OF CHILDREN

In case of overdose, get medical help or contact a Poison Control Center right away.

DIRECTIONS

- shake well before using
- all dosages may be repeated as needed, after meals and at bedtime
- fill enclosed dropper to recommended dosage level
- dispense liquid slowly into baby's mouth, toward the inner cheek
- may mix with 1 oz. of cool water, infant formula or other suitable liquids
- clean dropper after each use and close the bottle to maintain child resistance

age (yr) | weight (lb) | dose
infants under 2 | under 24 | 0.3 mL
children over 2 | over 24 | 0.6 mL

OTHER INFORMATION

store at room temperature

INACTIVE INGREDIENT SECTION

benzoic acid, flavor, magnesium aluminum silicate, purified water, simethicone emulsion, sorbitol, xanthan gum.

PRINCIPAL DISPLAY PANEL

Harris Teeter™

NDC 69256-520-09

INFANTS'

GAS RELIEF DROPS

Antigas

Simethicone 20 mg

Fast Relief of Gas Symptoms

No Artificial Flavor

Alcohol Free

Dye Free

Gentle & Safe**

Compare to the Active Ingredient in Mylicon®

Non-Staining Infants' Drops*

**Use only as directed;

do not exceed 12 doses per day.

1 FL OZ (30mL)